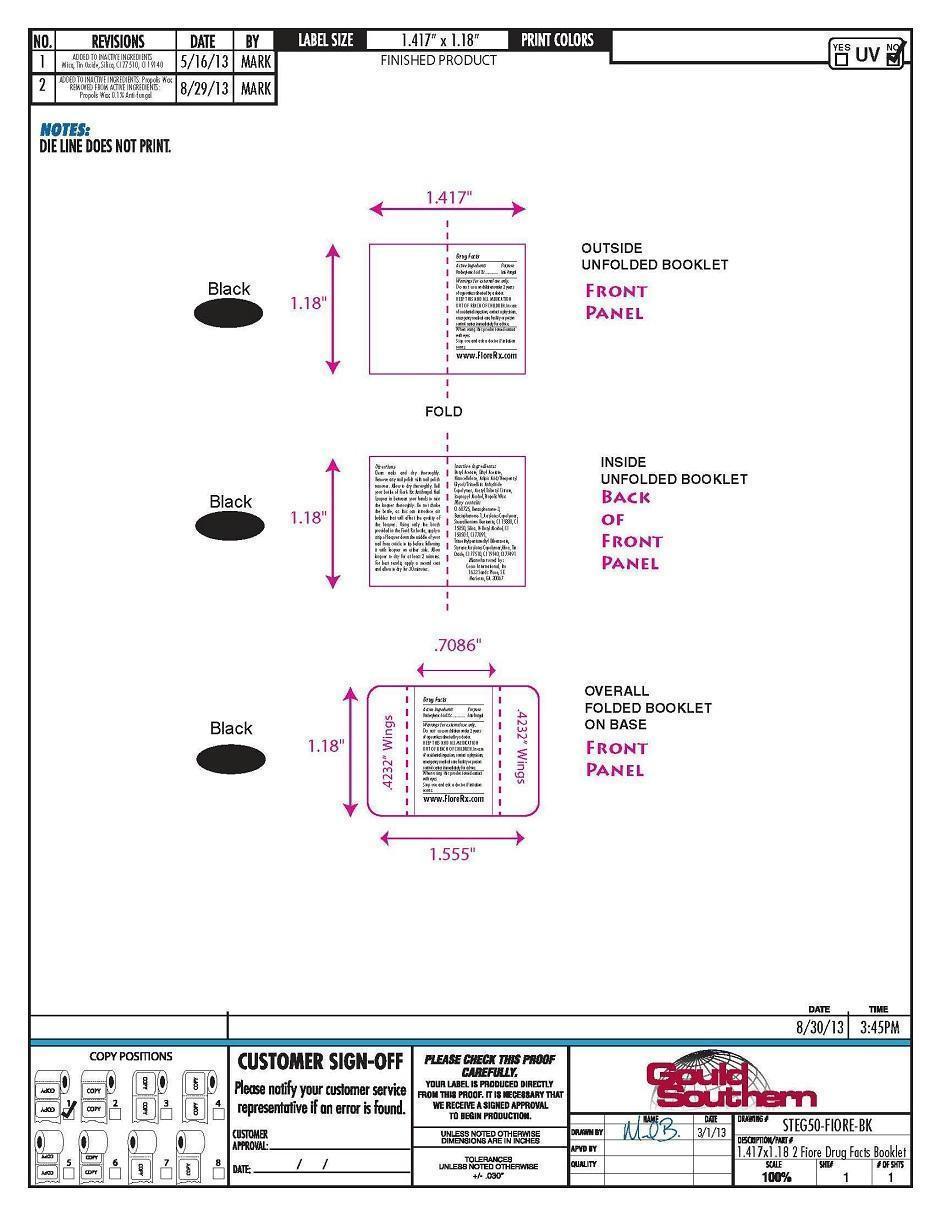 DRUG LABEL: Fiore Rx Eggplant My Garden Antifungal Nail Polish
NDC: 52261-0205 | Form: FILM
Manufacturer: Cosco International, Inc.
Category: otc | Type: HUMAN OTC DRUG LABEL
Date: 20130919

ACTIVE INGREDIENTS: Undecylenic Acid 0.45 g/15 mL
INACTIVE INGREDIENTS: Butyl Acetate 5.756907 g/15 mL; Ethyl Acetate 3.245433 g/15 mL; Pyroxylin 2.0149005 g/15 mL; POLYESTER-10 1.02544425 g/15 mL; ACETYLTRIBUTYL CITRATE 1.00744995 g/15 mL; ISOPROPYL ALCOHOL 0.86352435 g/15 mL; BENTOQUATAM 0.1727049 g/15 mL; DIMETHYLAMINOETHYL METHACRYLATE - BUTYL METHACRYLATE - METHYL METHACRYLATE COPOLYMER 0.16190535 g/15 mL; Polacrilin 0.0719628 g/15 mL; D&C RED NO. 34 0.061047 g/15 mL; TITANIUM DIOXIDE 0.046512 g/15 mL; FERRIC AMMONIUM FERROCYANIDE 0.034884 g/15 mL; SILICON DIOXIDE 0.0287793 g/15 mL; Benzoresorcinol 0.0287793 g/15 mL; PROPOLIS WAX 0.015 g/15 mL; TRIMETHYLPENTANEDIYL DIBENZOATE 0.01438965 g/15 mL; FD&C YELLOW NO. 5 0.0002325 g/15 mL; D&C RED NO. 6 0.00014535 g/15 mL

Drug Facts

Active Ingredient Purpose
Undecylenic Acid 3%........................Anti-fungal

PURPOSE

Anti-fungal

Warnings For external use only.

Do not use on children under 2 years of age unless directed by a doctor.
KEEP THIS AND ALL MEDICATION OUT OF REACH OF CHILDREN.In case of accidental ingestion, contact a physician, emergency medical care facility or poison control center immediately for advice.

When using this product avoid contact with eyes.

Stop use and ask a doctor if irritation occurs.

Directions:

Clean nails and dry thoroughly.
Remove any nail polish with nail
polish remover. Allow to dry
thoroughly. Roll your bottle of Fioré
Rx Antifungal Nail Lacquer in between
your hands to mix the lacquer
thoroughly. Do not shake the bottle,
as this can introduce air bubbles that
will affect the quality of the lacquer.
Using only the brush provided in the
Fioré Rx bottle, apply a strip of
lacquer down the middle of your nail
from cuticle to tip before following it
with lacquer on either side. Allow
lacquer to dry for at least 2 minutes.
For best results, apply a second coat
and allow to dry for 30 minutes.

Inactive ingredients:

Butyl acetate, ethyl acetate, nitrocellulose, adipic acid/neopentyl glycol/trimellitic copolymer anhydride, acetyl tributyl citrate, isopropyl alcohol, propolis wax

May contain:

CI 60725, Benzophenone-3,

Bensophenone-1, Acrylates Copolymer,

Stearalkonium Bentonite, CI 15880, CI

15850, Silica, N-Butyl Alcohol, CI

15850:1, CI 77891,

Trimethylpentanediyl Dibenzoate,

Styrene Acrylates Copolymer,Mica, Tin

Oxide, CI 77510, CI 19140, CI 77491